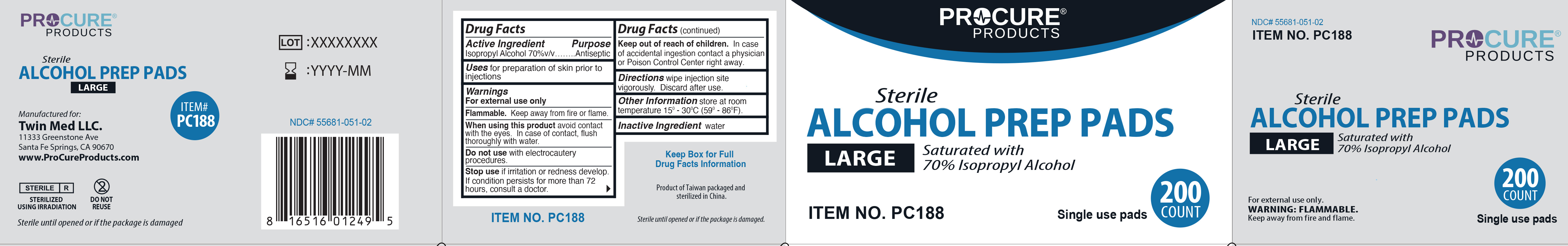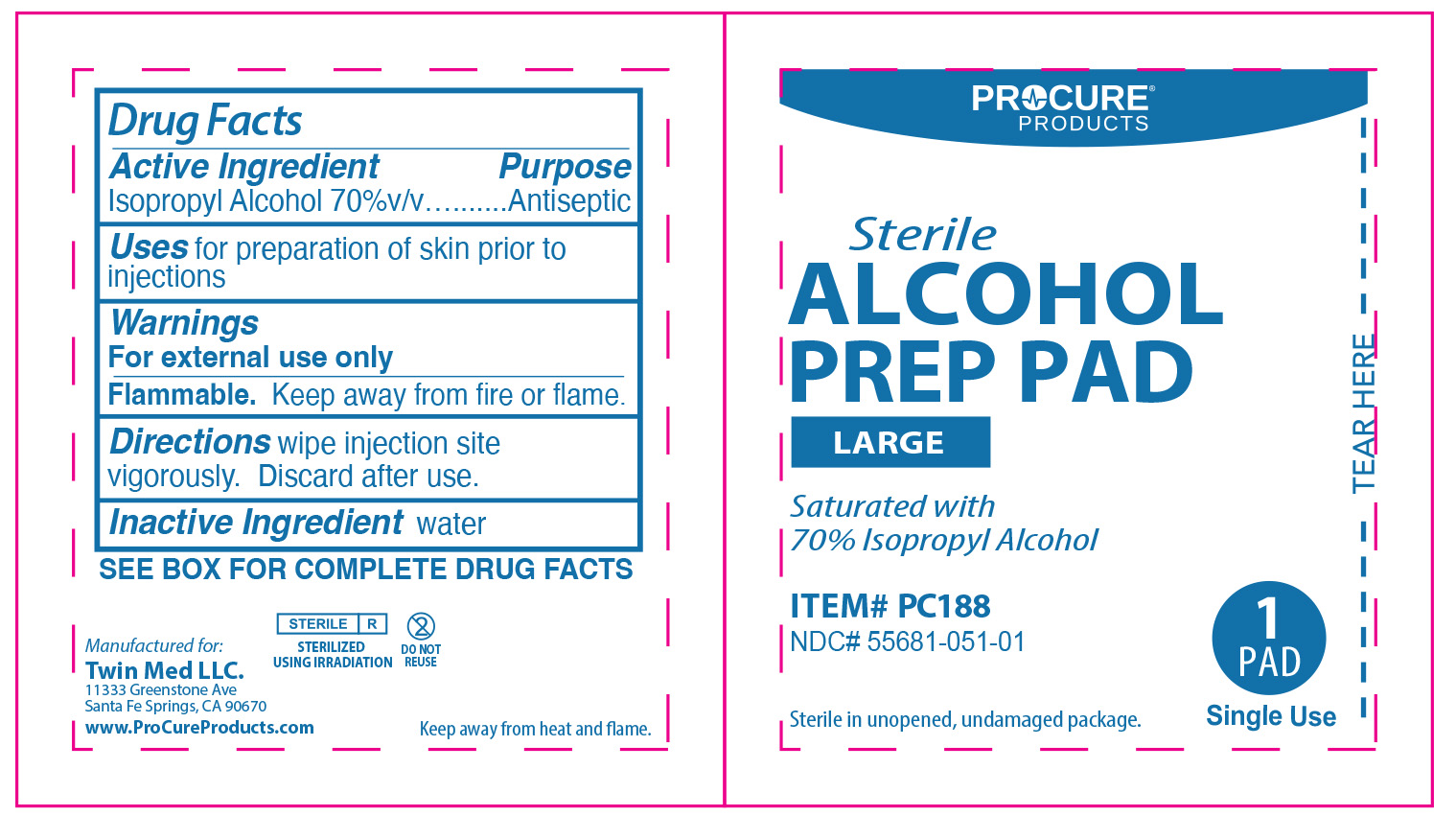 DRUG LABEL: ProCure Alcohol Prep Pads
NDC: 55681-051 | Form: CLOTH
Manufacturer: Twin Med LLC
Category: otc | Type: HUMAN OTC DRUG LABEL
Date: 20250930

ACTIVE INGREDIENTS: ISOPROPYL ALCOHOL .7 mL/1 1
INACTIVE INGREDIENTS: WATER

Active Ingredient

Isopropyl Alcohol 70% v/v

Purpose

Antiseptic

Uses

For preparation of skin prior to injection

Warnings

For external use only

Flammable. Keep away from fire or flame.

When using this product, avoid contact with the eyes. In case of contact, flush thoroughly with water.

Do not use with electrocautery procedures

Stop use if irritation or redness develop. If condition persists for more than 72 hours, consult a doctor

Keep out of reach of children. In case of accidental ingestion contact a physician or Poison Control Center right away.

Directions

Wipe injection site vigorously. Discard after use.

Inactive Ingredient

Water